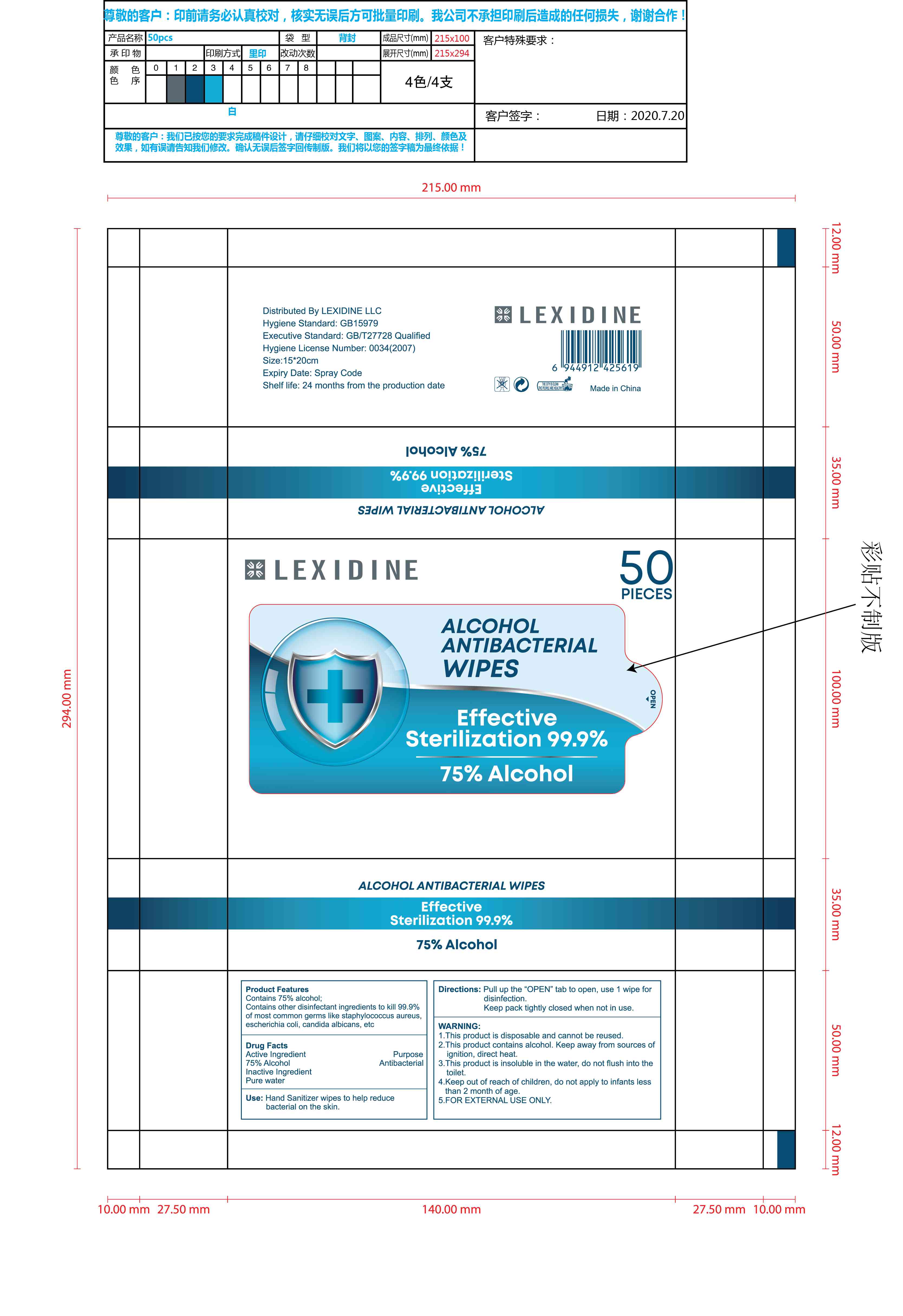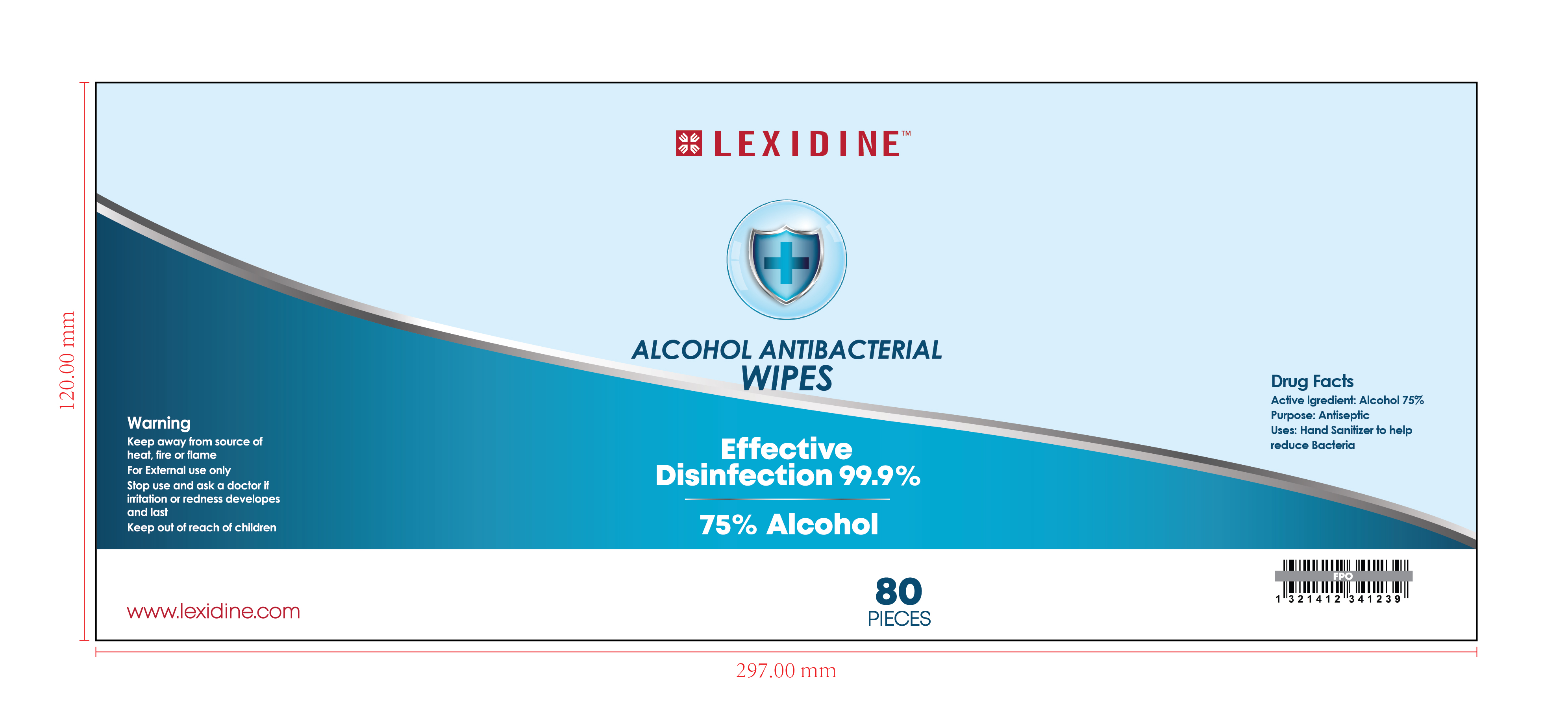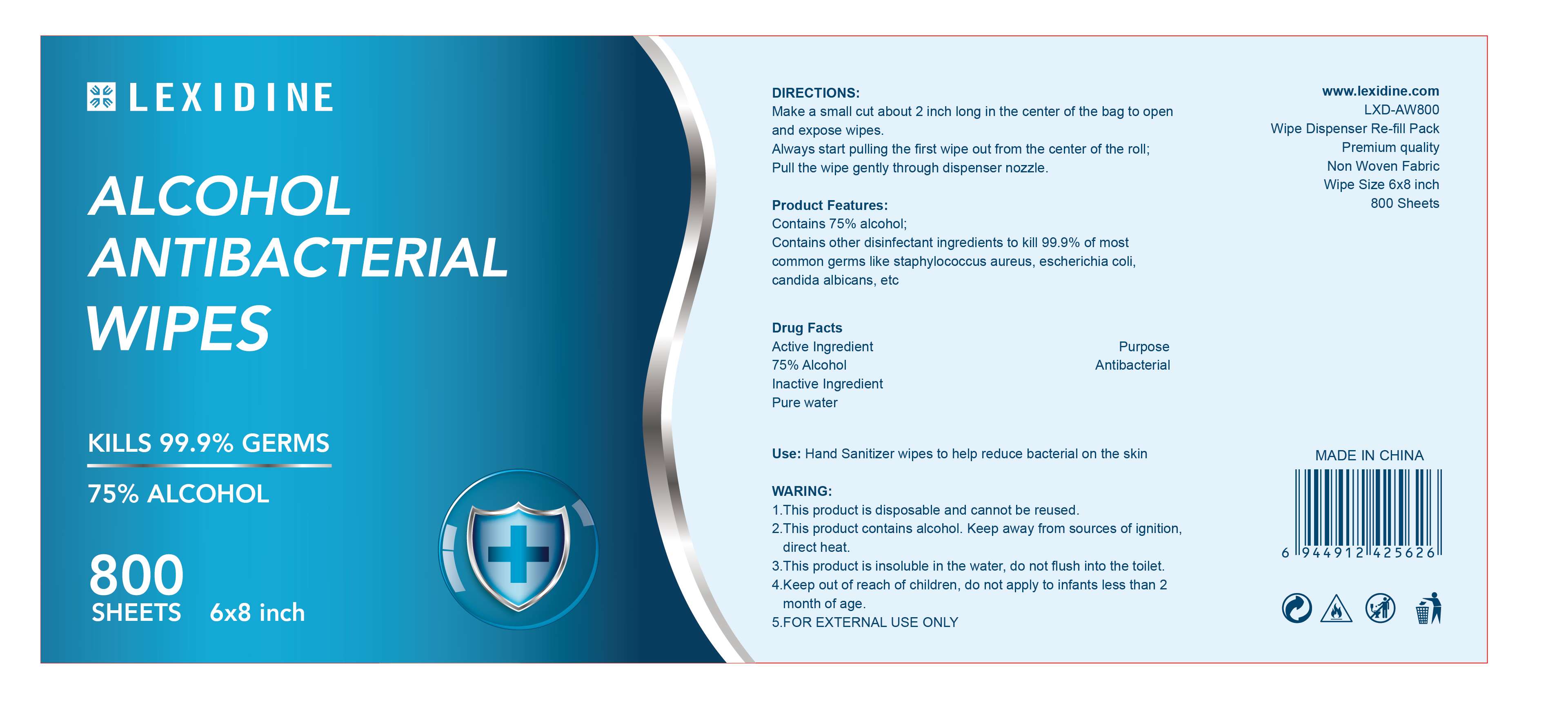 DRUG LABEL: LEXIDINE ALCOHOL ANTIBACTERIAL WIPES
NDC: 78183-033 | Form: CLOTH
Manufacturer: Kunming Ansheng Industry & Trade Co., Ltd.
Category: otc | Type: HUMAN OTC DRUG LABEL
Date: 20200824

ACTIVE INGREDIENTS: ALCOHOL 75 1/100 1
INACTIVE INGREDIENTS: WATER

78183-033
LEXIDINE ALCOHOL ANTIBACTERIAL WIPES

Active Ingredient(s)

75% Alcohol

Purpose

Antibacterial

Use

Hand Sanitizer wipes to help reduce bacterial on the skin

Contains 75% alcohol;
Contains other disinfectant ingredients to kill 99.9% of most common germs like staphylococcus aureus, escherichia coli, candida albicans, etc

Warnings

1.This product is disposable and cannot be reused.
2.This product contains alcohol. Keep away from sources of ignition, direct heat.
3.This product is insoluble in the water, do not flush into the toilet.
4.Keep out of reach of children, do not apply to infants less than 2 month of age.
5.FOR EXTERNAL USE ONLY

Do not use

/

WHEN USING

1.This product is disposable and cannot be reused.
2.This product contains alcohol. Keep away from sources of ignition, direct heat.
3.This product is insoluble in the water, do not flush into the toilet.
4.Keep out of reach of children, do not apply to infants less than 2 month of age.

STOP USE

/

Keep out of reach of children, do not apply to infants less than 2 month of age.

Directions

Make a small cut about 2 inch long in the center of the bag to open and expose wipes.
Always start pulling the first wipe out from the center of the roll;
Pull the wipe gently through dispenser nozzle.

Other information

/

Inactive ingredients

Pure water